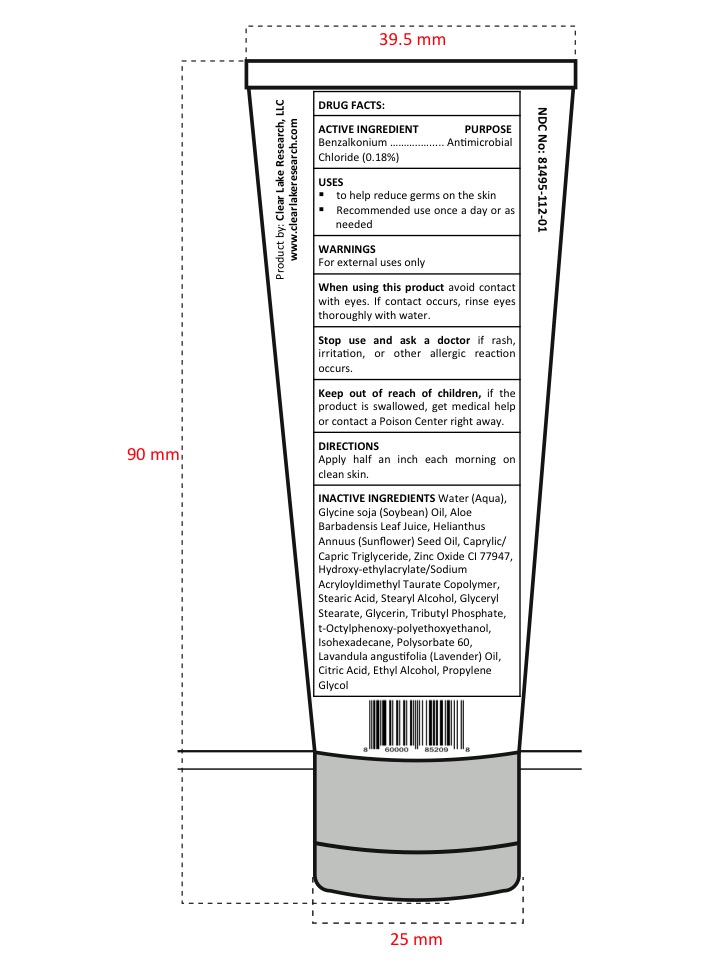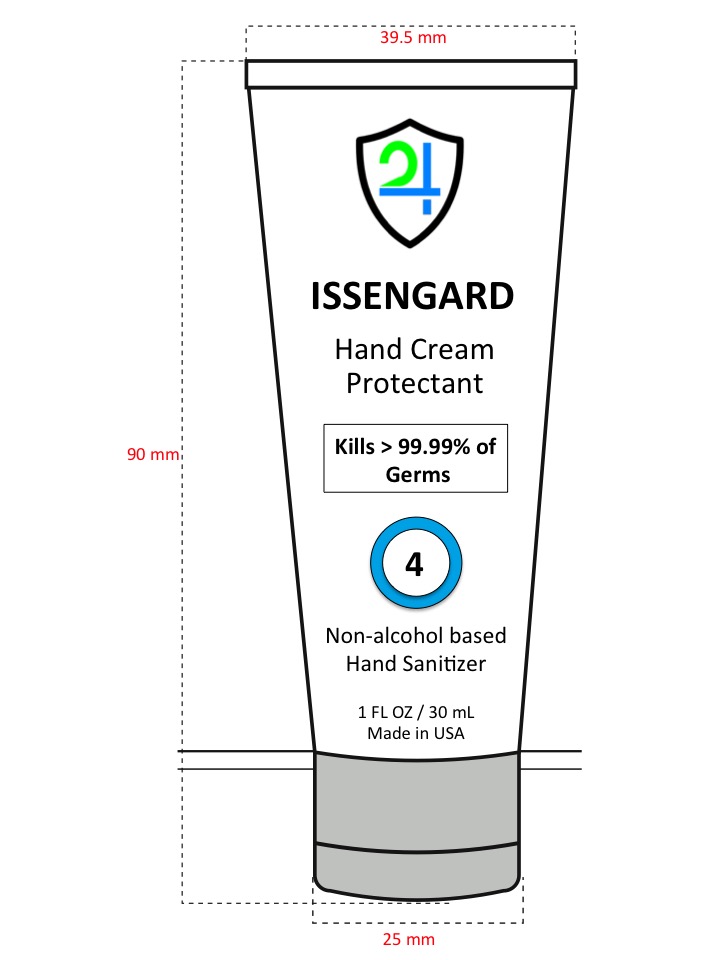 DRUG LABEL: ISSENGARD 24 HAND SANITIZER 3 oz
NDC: 81495-112 | Form: CREAM
Manufacturer: CLEAR LAKE RESEARCH, LLC
Category: otc | Type: HUMAN OTC DRUG LABEL
Date: 20221229

ACTIVE INGREDIENTS: BENZALKONIUM CHLORIDE 0.18 mg/100 mL
INACTIVE INGREDIENTS: POLYSORBATE 60; HYDROXYETHYL ACRYLATE/SODIUM ACRYLOYLDIMETHYL TAURATE COPOLYMER (45000 MPA.S AT 1%); ISOHEXADECANE; PROPYLENE GLYCOL; MEDIUM-CHAIN TRIGLYCERIDES; STEARYL ALCOHOL; GLYCERYL MONOSTEARATE; ZINC OXIDE; GLYCERIN; OCTOXYNOL-1; ALCOHOL; SOYBEAN OIL; LAVENDER OIL; SUNFLOWER OIL; TRI-N-BUTYL PHOSPHATE; WATER; ALOE VERA LEAF; STEARIC ACID; ANHYDROUS CITRIC ACID

Active Ingredient

Benzalkonium Chloride 0.18%

Purpose section

Antimicrobial

Warnings

For external uses only

Drug Facts

When using this product avoid contact with eyes. If contact occurs, rinse eyes thoroughly with water.

Stop use and ask a doctor if rash, irritation, or other allergic reaction occurs

Keep out of reach of children, if the product is swallowed, get medical help or contact a Poison Center right away.

Uses

- to help reduce germs on the skin
- Recommended use once a day or as needed

Directions

Apply half an inch each morning on clean skin.

Inactive Ingredients

Water (Aqua), Glycine soja (Soybean) Oil, Aloe Barbadensis Leaf Juice, Helianthus Annuus (Sunflower) Seed Oil, Caprylic/Capric Triglyceride, Tributyl Phosphate, Glycerin, t-Octylphenoxy-polyethoxyethanol, Hydroxy-ethylacrylate/Sodium Acryloyldimethyl Taurate, Copolymer, Isohexadecane, Polysorbate 60, Glyceryl Stearate, Stearic Acid, Stearyl Alcohol, Lavandula angustifolia (Lavender) Oil, Propylene Glycol, Ethyl Alcohol, Zinc Oxide CI 77947

Principal Display Panel - 30 mL

ISSENGARD

Hand Cream Protectant

Kills > 99.99% of Germs

Non-alcohol HAND SANITIZER

1 FL OZ / 30 mL

Made in USA